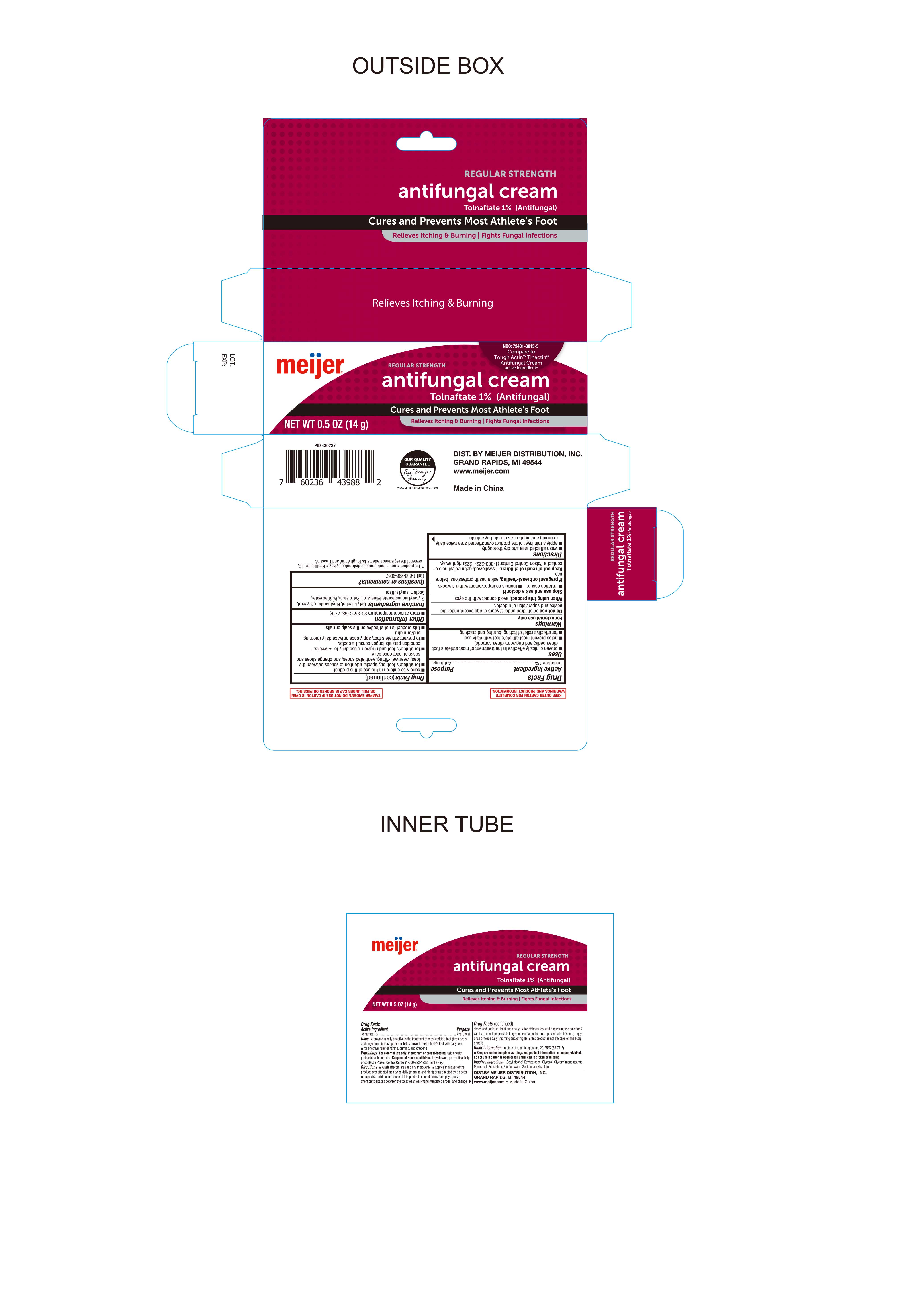 DRUG LABEL: Antifungal Cream Tolnaftate 1%
NDC: 79481-0015 | Form: CREAM
Manufacturer: Meijer
Category: otc | Type: HUMAN OTC DRUG LABEL
Date: 20230111

ACTIVE INGREDIENTS: TOLNAFTATE 1 g/100 g
INACTIVE INGREDIENTS: CETYL ALCOHOL; ETHYLPARABEN; GLYCERIN; MINERAL OIL; GLYCERYL MONOSTEARATE; PETROLATUM; WATER; SODIUM LAURYL SULFATE

Meijer Antifungal Cream Tolnaftate 1%

Active ingredient

Tolnaftate 1%

Purpose

Antifungal

Keep out of reach of children. If swallowed, get medical help or contact a Poison Control Center (1-800-222-1222) right away.

Uses

● proven clinically effective in the treatment of most athlete's foot (tinea pedis), and ringworm (tinea corporis) ● helps prevent most athlete's foot with daily use ● for effective relief of itching, burning and cracking.

Warnings

For external use only.

When using this product

Avoid contact with the eyes

Do not use on children under 2 years of age except under the advice and supervision of a doctor.

Stop Use and Ask a Doctor if

- irritation occurs
- there is no improvement within 4 weeks

If Pregnant or Breast-feeding ask a health professional before use

Inactive ingredients

Cetostearyl alcohol, ethylparaben, glycerol, mineral oil, glyceryl monostearate, petrolatum, purified water, sodium lauryl sulfate

Directions

● wash affected area and dry thoroughly

● apply a thin layer over affected area twice daily (morning and night) or as directed by a doctor

● supervise children in the use of this product

● for athlete’s foot: pay special attention to spaces between the toes, wear well-fitting ventilated shoes and change shoes and socks at least once daily.

● for athlete's foot and ringworm, use daily for 4 weeks. If condition persists longer, consult doctor.

● to prevent athlete's foot, apply once or twice daily (morning and/or night)

● this product is not effective on the scalp or nails.

Other information

● store between 20° to 25°C (68° to 77°F)

Questions or Comments?

1-888-296-9067

Distributed By

Distrubuted By Meijer Distribution, Inc.

Grand Rapids, MI 49544

www.meijer.com

Made in China

This product is not manufactured or distributed by Bayer Healthcare LLC, owner of the registered trademarks Tough Actin and Tinactin.